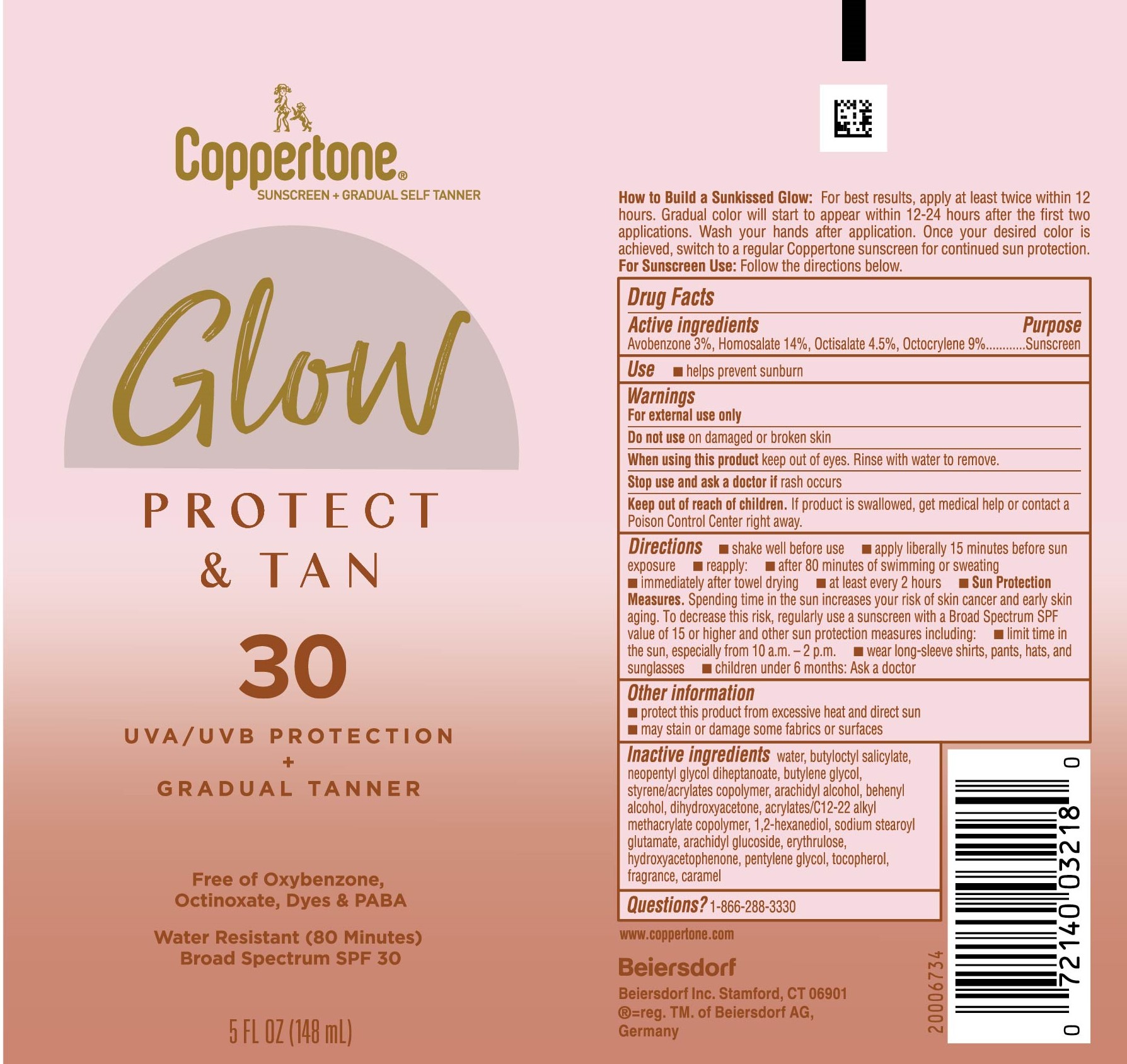 DRUG LABEL: Coppertone Protect and Tan SPF 30
NDC: 66800-0082 | Form: LOTION
Manufacturer: Beiersdorf Inc
Category: otc | Type: HUMAN OTC DRUG LABEL
Date: 20251231

ACTIVE INGREDIENTS: AVOBENZONE 3 g/100 g; OCTOCRYLENE 9 g/100 g; OCTISALATE 4.5 g/100 g; HOMOSALATE 14 g/100 g
INACTIVE INGREDIENTS: BUTYLENE GLYCOL; STYRENE/ACRYLAMIDE COPOLYMER (MW 500000); ARACHIDYL ALCOHOL; FRAGRANCE FRESH CITRUS FLORAL ORC1501495; HYDROXYACETOPHENONE; 1,2-HEXANEDIOL; TOCOPHEROL; WATER; CARAMEL; L-ERYTHRULOSE; ALLYL METHACRYLATE; BUTYLOCTYL SALICYLATE; NEOPENTYL GLYCOL DIHEPTANOATE; PENTYLENE GLYCOL; DOCOSANOL; DIHYDROXYACETONE; SODIUM STEAROYL GLUTAMATE; ARACHIDYL GLUCOSIDE

Protect & Tan Gradual Tanner SPF 30

Active ingredients

Avobenzone 3%, Homosalate 14%, Octisalate 4.5%, Octocrylene 9%

Purpose

Sunscreen

Use

■ helps prevent sunburn

Warnings

For external use only

Do not useon damaged or broken skin

WHEN USING

When using this productkeep out of eyes. Rinse with water to remove.

Stop use and ask a doctor ifrash occurs

Keep out of reach of children.If product is swallowed, get medical help or contact a Poison Control Center right away.

Directions

■ shake well before use

■ apply liberally 15 minutes before sun exposure

■ reapply:

■ after 80 minutes of swimming or sweating

■ immediately after towel drying

■ at least every 2 hours

■ Sun Protection Measures. Spending time in the sun increases your risk of skin cancer and early skin aging. To decrease this risk, regularly use a sunscreen with a Broad Spectrum SPF value of 15 or higher and other sun protection measures including:

■ limit time in the sun, especially from 10 a.m. – 2 p.m.

■ wear long-sleeve shirts, pants, hats, and sunglasses

■ children under 6 months: Ask a doctor

Other information

■ protect this product from excessive heat and direct sun

■ may stain or damage some fabrics or surfaces

Inactive ingredients

water, butyloctyl salicylate, neopentyl glycol diheptanoate, butylene glycol, styrene/acrylates copolymer, arachidyl alcohol, behenyl alcohol, dihydroxyacetone, acrylates/C12-22 alkyl methacrylate copolymer, 1,2-hexanediol, sodium stearoyl glutamate, arachidyl glucoside, erythrulose, hydroxyacetophenone, pentylene glycol, tocopherol, fragrance, caramel

Questions?

1-866-288-3330

PACKAGE LABEL

Coppertone® Sunscreen + Self Tanner

Glow

Protect & Tan 30

UVA/UVB Protection + Gradual Tanner

Free of Oxybenzone, Octinoxate, Dyes & PABA

Water Resistant (80 Minutes)

Broad Spectrum SPF 30

5 FL OZ (148 mL)